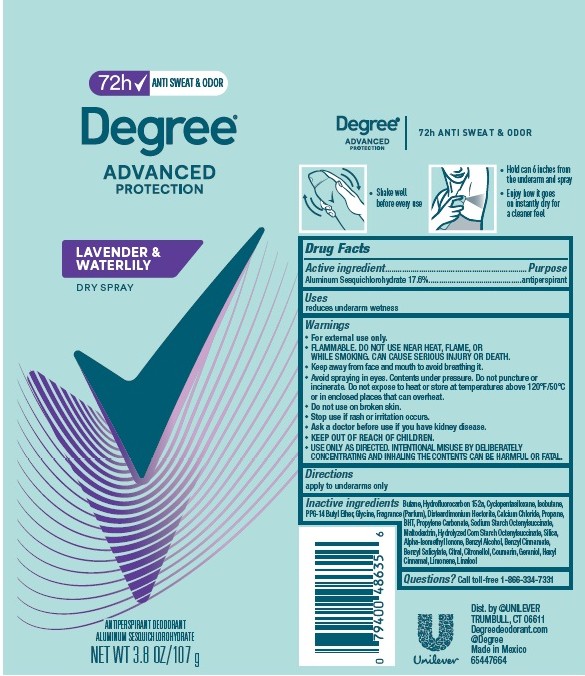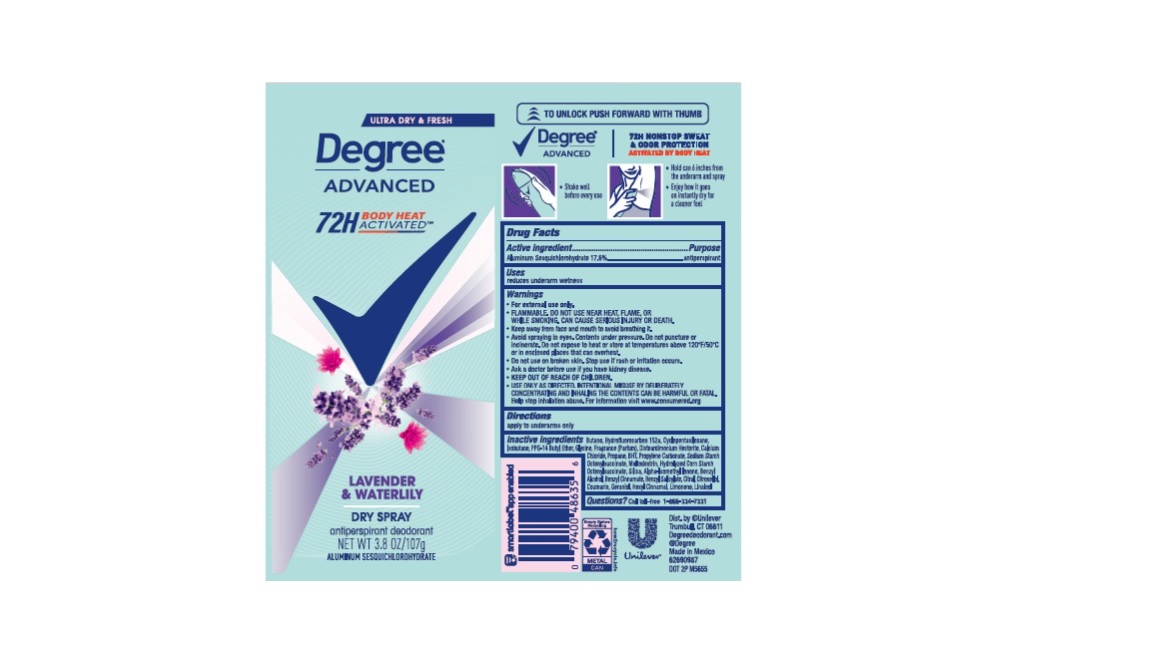 DRUG LABEL: Degree
NDC: 64942-2211 | Form: AEROSOL, SPRAY
Manufacturer: Conopco, Inc. d/b/a Unilever
Category: otc | Type: HUMAN OTC DRUG LABEL
Date: 20260212

ACTIVE INGREDIENTS: ALUMINUM SESQUICHLOROHYDRATE 17.6 g/100 g
INACTIVE INGREDIENTS: BENZYL ALCOHOL; BENZYL SALICYLATE; CITRAL; SILICON DIOXIDE; MALTODEXTRIN; PROPYLENE CARBONATE; GLYCINE; LIMONENE, (+)-; ISOBUTANE; .BETA.-CITRONELLOL, (R)-; BUTANE; 1,1-DIFLUOROETHANE; CYCLOMETHICONE 5; PPG-14 BUTYL ETHER; DISTEARDIMONIUM HECTORITE; CALCIUM CHLORIDE; LINALOOL, (+/-)-; PROPANE; BUTYLATED HYDROXYTOLUENE; BENZYL CINNAMATE; ISOMETHYL-.ALPHA.-IONONE; .ALPHA.-HEXYLCINNAMALDEHYDE; COUMARIN; GERANIOL

Degree Advanced Lavender & Waterlily Dry Spray 72H Antiperspirant Deodorant

Drug Facts

Active ingredient

Aluminum Sesquichlorohydrate (17.6%)

Purpose

antiperspirant

Uses

reduces underarm wetness

Directions

For underarms use only

Inactive ingredients

Butane, Hydrofluorocarbon 152a, Cyclopentasiloxane, Isobutane, PPG-14 Butyl Ether, Glycine, Fragrance (Parfum), Disteardimonium Hectorite, Calcium Chloride, Propane, Sodium Starch Octenylsuccinate, BHT, Propylene Carbonate, Maltodextrin, Hydrolyzed Corn Starch Octenylsuccinate, Silica, Alpha-Isomethyl Ionone, Benzyl Alcohol, Benzyl Cinnamate, Benzyl Salicylate. Citral, Citronellol, Coumarin, Geraniol, Hexyl Cinnamal, Limonene, Linalool

Questions?

Call toll-free 1-866-334-7331